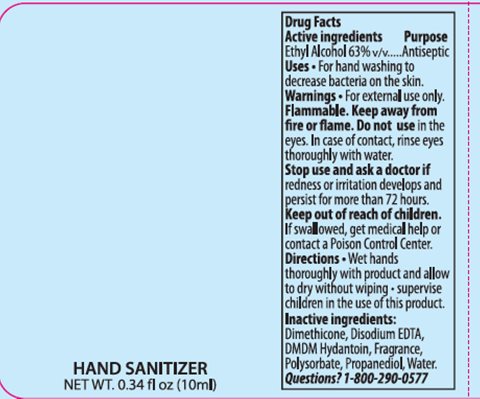 DRUG LABEL: Sanell Hand Sanitizer
NDC: 63645-174 | Form: SPRAY
Manufacturer: OraLabs
Category: otc | Type: HUMAN OTC DRUG LABEL
Date: 20250428

ACTIVE INGREDIENTS: ALCOHOL 6.3 mL/10 mL
INACTIVE INGREDIENTS: WATER 3.581 mL/10 mL

Drug Facts

Active ingredient

Ethyl Alcohol 63.00%

Purpose

Antiseptic

Keep Out of Reach of Children

If swallowed get medical help or contact a Poison Control Center right away.

Uses

For handwashing to decrease bacteria on the skin.

Warnings

For external use only: Hands. Flammable. Keep away from fire or flame. Do not use in the eyes. In case of contact, rinse eyes thoroughly with water. Stop use and ask a doctor: if irritation and redness develop and persists for more than 72 hours.

Directions

Wet hands thoroughly with product and allow to dry without wiping. Supervise children in the use of this product.

Inactive Ingredients

Dimethicone, Disodium EDTA, DMDM Hydantoin, Fragrance, Polysorbate 20, Propanediol, Water.